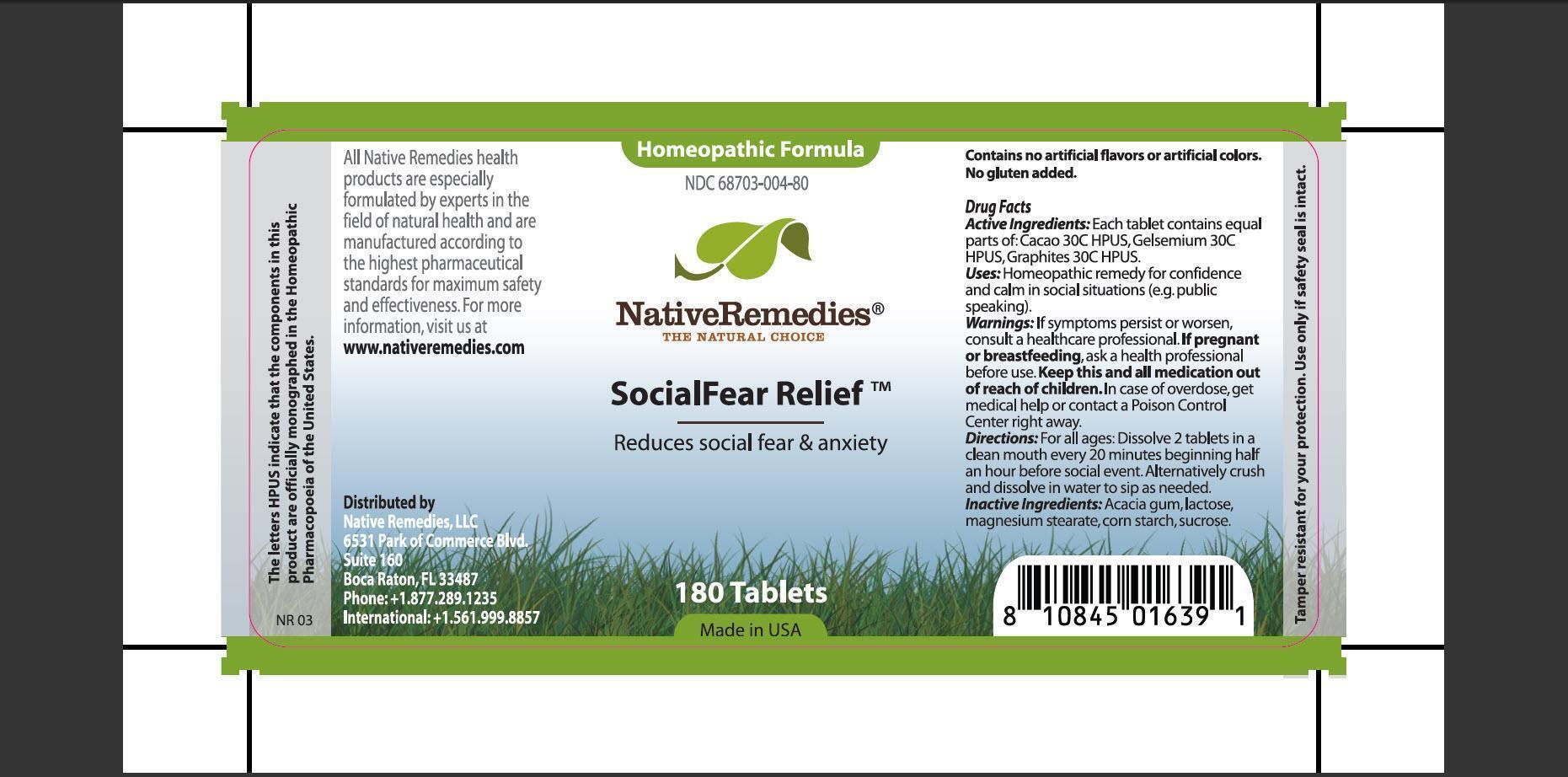 DRUG LABEL: SocialFear Relief
NDC: 68703-004 | Form: TABLET
Manufacturer: Native Remedies, LLC
Category: homeopathic | Type: HUMAN OTC DRUG LABEL
Date: 20130117

ACTIVE INGREDIENTS: COCOA 30 [hp_C]/1 1; GELSEMIUM SEMPERVIRENS ROOT 30 [hp_C]/1 1; GRAPHITE  30 [hp_C]/1 1
INACTIVE INGREDIENTS: ACACIA; LACTOSE; MAGNESIUM STEARATE; STARCH, CORN; SUCROSE

SocialFear Relief

PURPOSE

Reduces social fear and anxiety

ACTIVE INGREDIENT

Active Ingredients: Each tablet contains equal parts of : Cacao 30C HPUS, Gelsemium 30C HPUS, Graphites 30C HPUS.

INDICATIONS AND USAGE

Uses: Homeopathic remedy for confidence and calm in social situations (e.g. public speaking)

WARNINGS

Warnings: If symptoms persist or worsen, consult a healthcare professional.

PREGNANCY OR BREAST FEEDING

If pregnant or breastfeeding, ask a health professional before use.

KEEP OUT OF REACH OF CHILDREN

Keep this and all medication out of reach of children.

OVERDOSAGE

In case of overdose, get medical help or contact a Poison Control center right away.

DOSAGE AND ADMINISTRATION

Directions: For all ages: Dissolve 2 tablets in a clean mouth every 20 minutes beginning half an hour before social event. Alternatively crush and dissolve in water to sip as needed.

INACTIVE INGREDIENT

Inactive Ingredients: Acacia gum, lactose, magnesium stearate, corn starch, sucrose.

PATIENT COUNSELING INFORMATION

The letters HPUS indicate that the components in this product are officially monographed in the Homeopathic Pharmacopoeia of the United States.

All Native Remedies health products are especially formulated by experts in the field of natural health and are manufactures according to the highest pharmaceutical standards for maximum safety and effectiveness. For more information, visit us at www.nativeremedies.com

Distributed by
Native Remedies, LLC
6531 Park of Commerce Blvd.
Suite 160
Boca Raton, Fl 33487
Phone:+1.877.289.1235
International:+1.561.999.8857

Contains no artificial flavors or artificial colors. No gluten added.

STORAGE AND HANDLING

Tamper resistant for your protection. Use only if safety seal is intact.